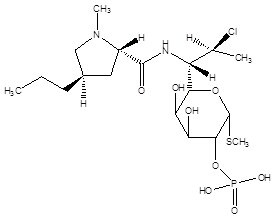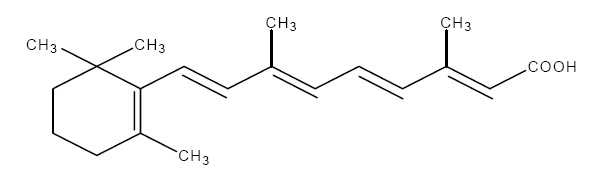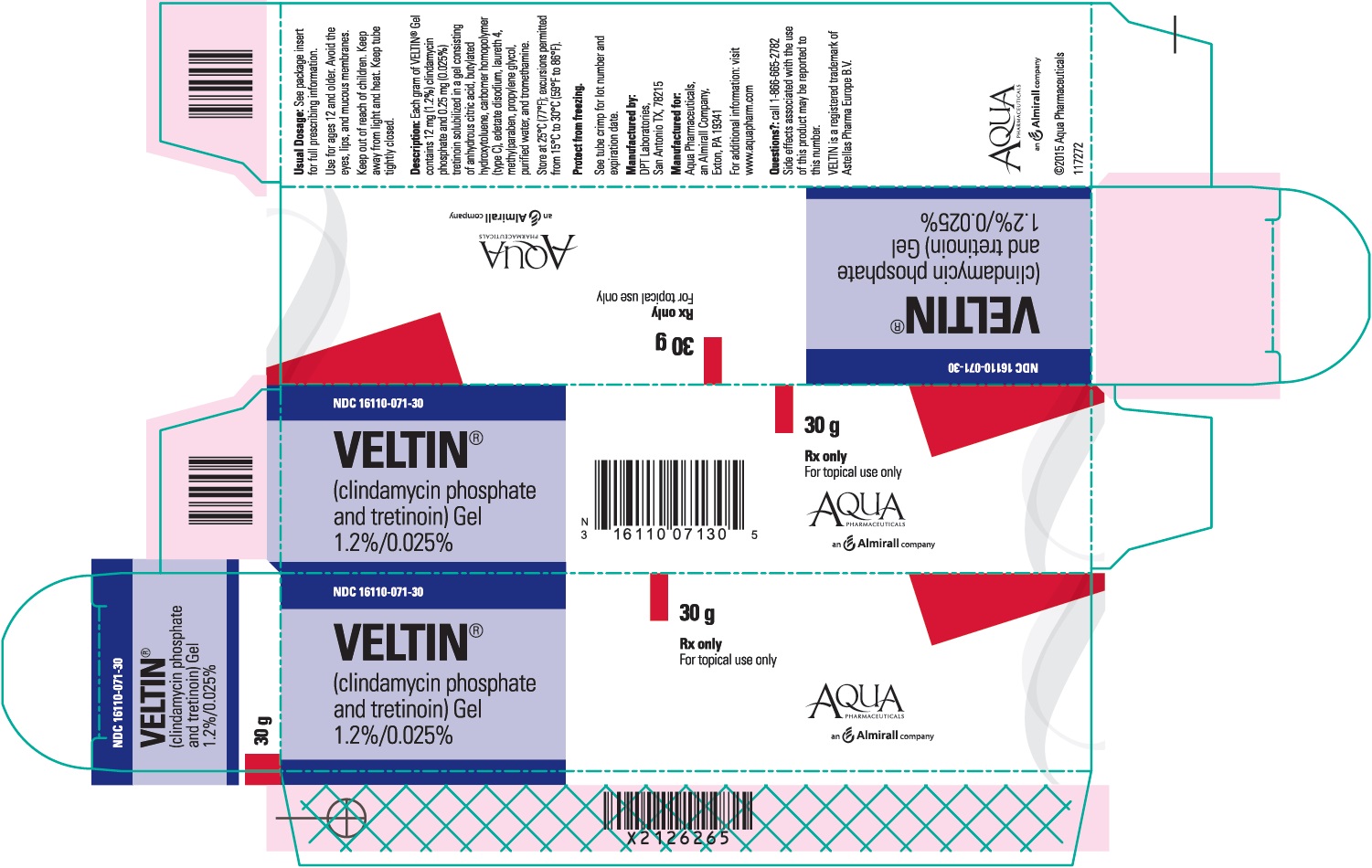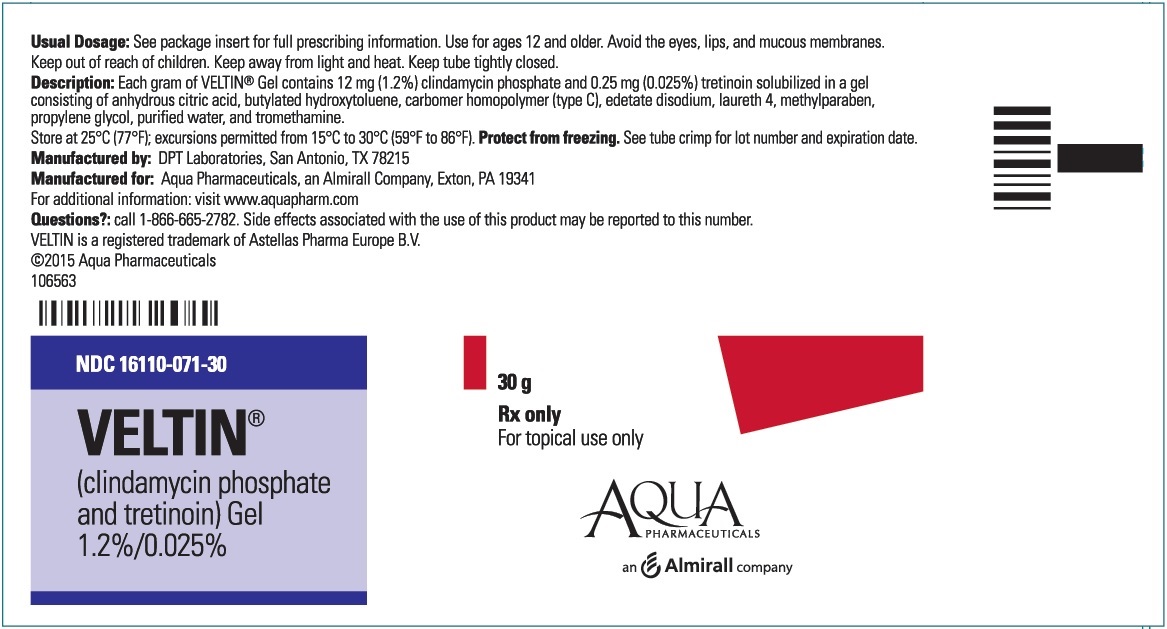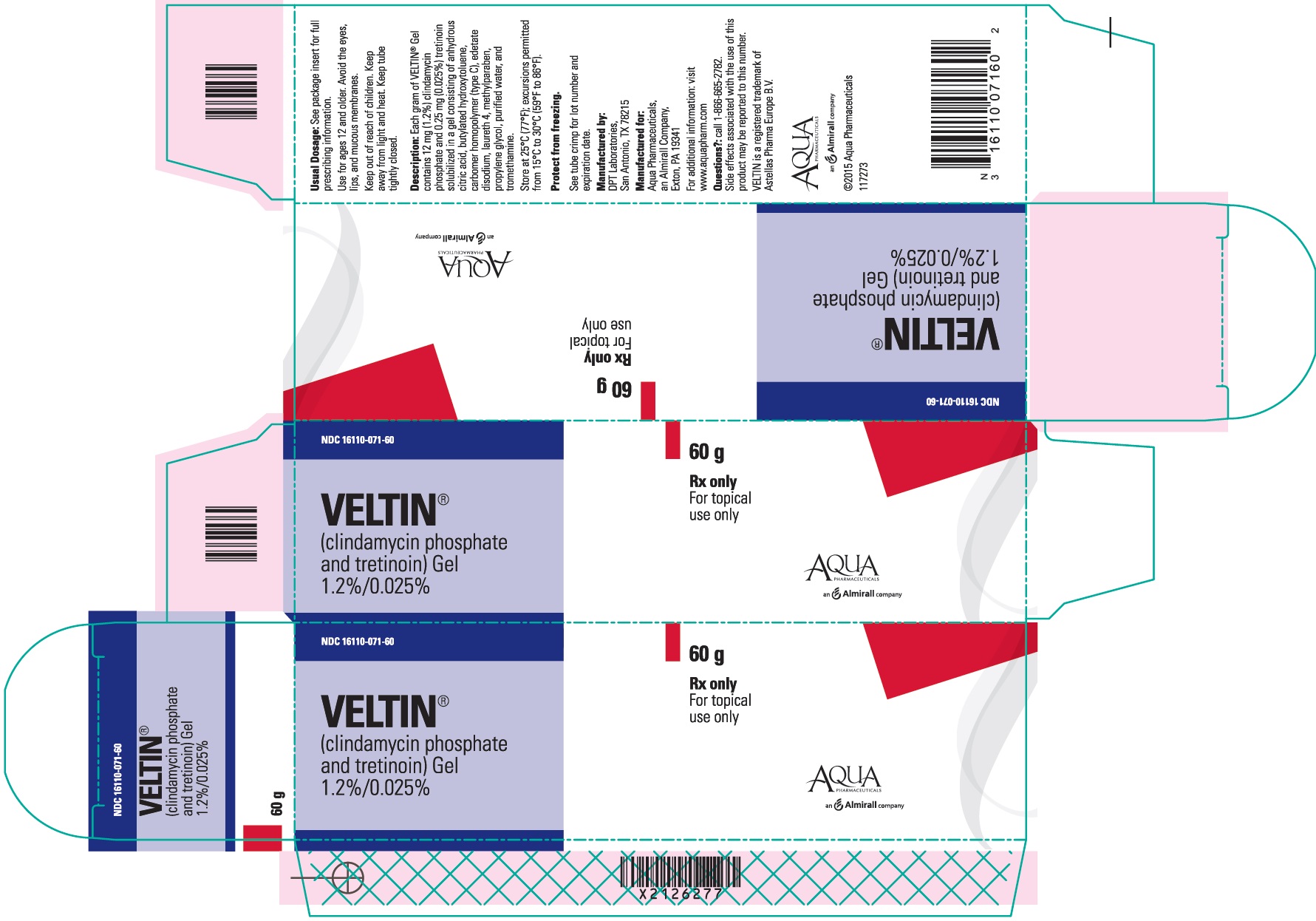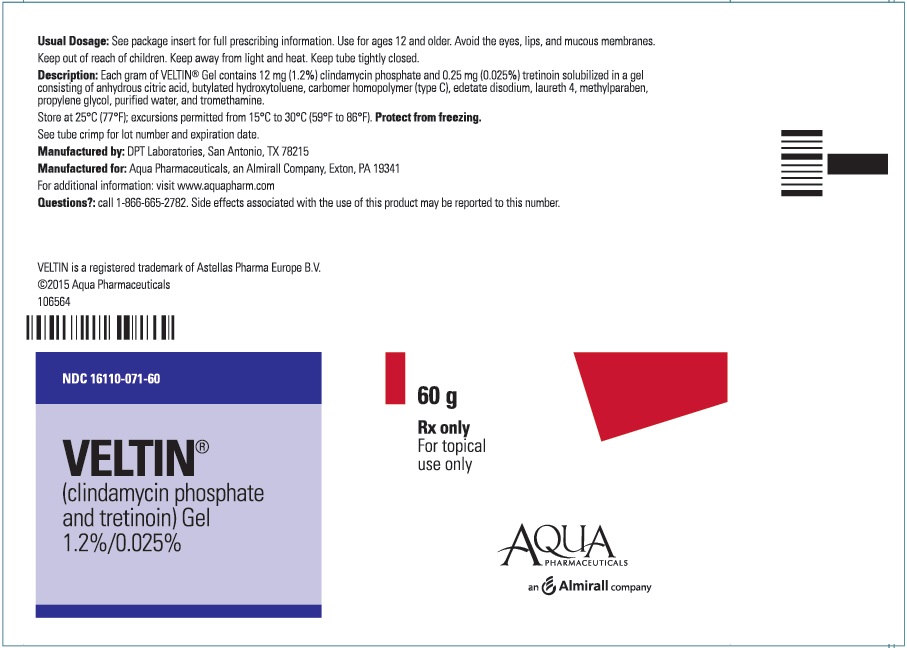 DRUG LABEL: VELTIN
NDC: 16110-071 | Form: GEL
Manufacturer: Almirall, LLC
Category: prescription | Type: HUMAN PRESCRIPTION DRUG LABEL
Date: 20210801

ACTIVE INGREDIENTS: CLINDAMYCIN PHOSPHATE 10 mg/1 g; TRETINOIN 0.25 mg/1 g
INACTIVE INGREDIENTS: BUTYLATED HYDROXYTOLUENE; CARBOMER HOMOPOLYMER TYPE C (ALLYL PENTAERYTHRITOL CROSSLINKED); ANHYDROUS CITRIC ACID; EDETATE DISODIUM; METHYLPARABEN; LAURETH-4; PROPYLENE GLYCOL; TROMETHAMINE; WATER

HIGHLIGHTS OF PRESCRIBING INFORMATION

These highlights do not include all the information needed to use VELTIN™ Gel safely and effectively. See full prescribing information for VELTIN Gel.
VELTIN™ (clindamycin phosphate and tretinoin) Gel 1.2%/0.025%
For topical use only
Initial U.S. Approval: 2006

1 INDICATIONS AND USAGE

- VELTIN™ Gel is a lincosamide antibiotic and retinoid combination product indicated for the topical treatment of acne vulgaris in patients 12 years and older. (1)

2 DOSAGE AND ADMINISTRATION

- Apply a pea-sized amount once daily in the evening lightly covering the entire affected area. Avoid the eyes, lips, and mucous membranes. (2)
- Not for oral, ophthalmic, or intravaginal use. (2)

3 DOSAGE FORMS AND STRENGTHS

- Topical gel: clindamycin phosphate 1.2% and tretinoin 0.025% in 30-gram and 60-gram tubes. (3)

4 CONTRAINDICATIONS

- VELTIN Gel is contraindicated in patients with regional enteritis, ulcerative colitis, or history of antibiotic-associated colitis. (4)

5 WARNINGS AND PRECAUTIONS

- Colitis: Clindamycin can cause severe colitis, which may result in death. Diarrhea, bloody diarrhea, and colitis (including pseudomembranous colitis) have been reported with the use of clindamycin. VELTIN Gel should be discontinued if significant diarrhea occurs. (5.1)
- Ultraviolet Light and Environmental Exposure: Avoid exposure to sunlight, sunlamps, and weather extremes. Wear sunscreen daily. (5.2)

6 ADVERSE REACTIONS

- Observed local treatment-related adverse reactions (≥ 1%) in clinical trials with VELTIN Gel were application site reactions, including dryness, irritation, exfoliation, erythema, pruritus, and dermatitis. Sunburn was also reported. (6.1)

To report SUSPECTED ADVERSE REACTIONS, contact Almirall at 1-866-665-2782 or FDA at 1-800-FDA-1088 or www.fda.gov/medwatch.

7 DRUG INTERACTIONS

- VELTIN Gel should not be used in combination with erythromycin-containing products because of its clindamycin component. (7.1)

8 USE IN SPECIFIC POPULATIONS

- Pediatric Use: The efficacy and safety have not been established in pediatric patients younger than 12 years. (8.4)

FULL PRESCRIBING INFORMATION

1 INDICATIONS AND USAGE

VELTIN™ (clindamycin phosphate and tretinoin) Gel, 1.2%/0.025% is indicated for the topical treatment of acne vulgaris in patients 12 years and older.

2 DOSAGE AND ADMINISTRATION

VELTIN Gel should be applied once daily in the evening, gently rubbing the medication to lightly cover the entire affected area. Approximately a pea-sized amount will be needed for each application. Avoid the eyes, lips, and mucous membranes.

VELTIN Gel is not for oral, ophthalmic, or intravaginal use.

3 DOSAGE FORMS AND STRENGTHS

VELTIN Gel, containing clindamycin phosphate 1.2% and tretinoin 0.025%, is a yellow, opaque topical gel. Each gram of VELTIN Gel contains, as dispensed, 10 mg (1%) clindamycin as clindamycin phosphate, and 0.25 mg (0.025%) tretinoin solubilized in an aqueous-based gel.

4 CONTRAINDICATIONS

VELTIN Gel is contraindicated in patients with regional enteritis, ulcerative colitis, or history of antibiotic-associated colitis.

5 WARNINGS AND PRECAUTIONS

5.1 Colitis

Systemic absorption of clindamycin has been demonstrated following topical use. Diarrhea, bloody diarrhea, and colitis (including pseudomembranous colitis) have been reported with the use of topical clindamycin. If significant diarrhea occurs, VELTIN Gel should be discontinued.

Severe colitis has occurred following oral or parenteral administration of clindamycin with an onset of up to several weeks following cessation of therapy. Antiperistaltic agents such as opiates and diphenoxylate with atropine may prolong and/or worsen severe colitis. Severe colitis may result in death.

Studies indicate a toxin(s) produced by clostridia is one primary cause of antibiotic-associated colitis. The colitis is usually characterized by severe persistent diarrhea and severe abdominal cramps and may be associated with the passage of blood and mucus. Stool cultures for Clostridium difficile and stool assay for C. difficile toxin may be helpful diagnostically.

5.2 Ultraviolet Light and Environmental Exposure

Exposure to sunlight, including sunlamps, should be avoided during the use of VELTIN Gel. Patients with sunburn should be advised not to use the product until fully recovered because of heightened susceptibility to sunlight as a result of the use of tretinoin. Patients who may be required to have considerable sun exposure due to occupation and those with inherent sensitivity to the sun should exercise particular caution. Daily use of sunscreen products and protective apparel (e.g., a hat) are recommended. Weather extremes, such as wind or cold, also may be irritating to patients under treatment with VELTIN Gel.

6 ADVERSE REACTIONS

6.1 Adverse Reactions in Clinical Trials

Because clinical trials are conducted under widely varying conditions, adverse reaction rates observed in clinical trials of a drug cannot be directly compared with rates in the clinical trials of another drug and may not reflect the rates observed in clinical practice.

The safety data reflect exposure to VELTIN Gel in 1,104 subjects with acne vulgaris. Subjects were 12 years and older and were treated once daily in the evening for 12 weeks. Adverse reactions that were reported in ≥1% of subjects treated with VELTIN Gel are presented in Table 1.

Table 1. Treatment-Related Adverse Reactions Reported by ≥1% of Subjects
 | VELTIN Gel N = 1,104; n (%) | Clindamycin Gel N = 1,091; n (%) | Tretinoin Gel N = 1,084; n (%) | Vehicle Gel N = 552; n (%)
Patients with at least one adverse reaction | 140 (13) | 38 (3) | 141 (13) | 17 (3)
Application site dryness | 64 (6) | 12 (1) | 62 (6) | 3 (1)
Application site irritation | 50 (5) | 4 (<1) | 57 (5) | 5 (1)
Application site exfoliation | 50 (5) | 2 (<1) | 56 (5) | 2 (<1)
Application site erythema | 40 (4) | 6 (1) | 39 (4) | 3 (1)
Application site pruritus | 26 (2) | 7 (1) | 23 (2) | 6 (1)
Sunburn | 11 (1) | 6 (1) | 7 (1) | 3 (1)
Application site dermatitis | 6 (1) | 0 (0) | 8 (1) | 1 (<1)

Local skin reactions actively assessed at baseline and end of treatment with a score >0 are presented in Table 2.

Table 2. Local Skin Reactions in Subjects Treated With VELTIN Gel
 | VELTIN Gel |  | Vehicle Gel
Local Reaction | Baseline; N = 476; (%) | End of Treatment; N = 409; (%) | Baseline; N = 219; (%) | End of Treatment; N = 209; (%)
Erythema | 24% | 21% | 31% | 35%
Scaling | 8% | 19% | 14% | 12%
Dryness | 11% | 22% | 18% | 13%
Burning | 8% | 13% | 8% | 4%
Itching | 17% | 15% | 22% | 14%

During the 12 weeks of treatment, each local skin reaction peaked at Week 2 and gradually reduced thereafter.

7 DRUG INTERACTIONS

7.1 Erythromycin

VELTIN Gel should not be used in combination with erythromycin-containing products due to possible antagonism to the clindamycin component. In vitrostudies have shown antagonism between these 2 antimicrobials. The clinical significance of this in vitroantagonism is not known.

7.2 Neuromuscular Blocking Agents

Clindamycin has been shown to have neuromuscular blocking properties that may enhance the action of other neuromuscular blocking agents. Therefore, VELTIN Gel should be used with caution in patients receiving such agents.

8 USE IN SPECIFIC POPULATIONS

8.1 Pregnancy

Pregnancy Category C.

There are no well-controlled studies in pregnant women treated with VELTIN Gel. VELTIN Gel should be used during pregnancy only if the potential benefit justifies the potential risk to the fetus. A limit teratology study performed in Sprague Dawley rats treated topically with VELTIN Gel or 0.025% tretinoin gel at a dose of 2 mL/kg during gestation days 6 to 15 did not result in teratogenic effects. Although no systemic levels of tretinoin were detected, craniofacial and heart abnormalities were described in drug-treated groups. These abnormalities are consistent with retinoid effects and occurred at 16 times the recommended clinical dose assuming 100% absorption and based on body surface area comparison. For purposes of comparison of the animal exposure to human exposure, the recommended clinical dose is defined as 1 g of VELTIN Gel applied daily to a 50-kg person.

Clindamycin: Reproductive developmental toxicity studies performed in rats and mice using oral doses of clindamycin up to 600 mg/kg/day (480 and 240 times the recommended clinical dose based on body surface area comparison, respectively) or subcutaneous doses of clindamycin up to 180 mg/kg/day (140 and 70 times the recommended clinical dose based on body surface area comparison, respectively) revealed no evidence of teratogenicity.
Tretinoin: Oral tretinoin has been shown to be teratogenic in mice, rats, hamsters, rabbits, and primates. It was teratogenic and fetotoxic in Wistar rats when given orally at doses greater than 1 mg/kg/day (32 times the recommended clinical dose based on body surface area comparison). However, variations in teratogenic doses among various strains of rats have been reported. In the cynomologous monkey, a species in which tretinoin metabolism is closer to humans than in other species examined, fetal malformations were reported at oral doses of 10 mg/kg/day or greater, but none were observed at 5 mg/kg/day (324 times the recommended clinical dose based on body surface area comparison), although increased skeletal variations were observed at all doses. Dose-related teratogenic effects and increased abortion rates were reported in pigtail macaques.

With widespread use of any drug, a small number of birth defect reports associated temporally with the administration of the drug would be expected by chance alone. Thirty cases of temporally associated congenital malformations have been reported during 2 decades of clinical use of another formulation of topical tretinoin. Although no definite pattern of teratogenicity and no causal association have been established from these cases, 5 of the reports describe the rare birth defect category, holoprosencephaly (defects associated with incomplete midline development of the forebrain). The significance of these spontaneous reports in terms of risk to fetus is not known.

8.3 Nursing Mothers

It is not known whether clindamycin is excreted in human milk following use of VELTIN Gel. However, orally and parenterally administered clindamycin has been reported to appear in breast milk. Because of the potential for serious adverse reactions in nursing infants, a decision should be made whether to discontinue nursing or to discontinue the drug, taking into account the importance of the drug to the mother. It is not known whether tretinoin is excreted in human milk. Because many drugs are excreted in human milk, caution should be exercised when VELTIN Gel is administered to a nursing woman.

8.4 Pediatric Use

Safety and effectiveness of VELTIN Gel in pediatric patients younger than 12 years have not been established.

Clinical trials of VELTIN Gel included 2,086 subjects aged 12 through 17 years with acne vulgaris. [See Clinical Studies (14).]

8.5 Geriatric Use

Clinical trials of VELTIN Gel did not include sufficient numbers of subjects aged 65 and older to determine whether they respond differently from younger subjects.

11 DESCRIPTION

VELTIN (clindamycin phosphate and tretinoin) Gel, 1.2%/0.025%, is a fixed combination of 2 solubilized active ingredients in an aqueous-based gel. Clindamycin phosphate is a water soluble ester of the semi-synthetic antibiotic produced by a 7(S)-chloro-substitution of the 7(R)-hydroxyl group of the parent antibiotic lincomycin.

The chemical name for clindamycin phosphate is methyl 7-chloro-6,7,8-trideoxy-6-(1-methyl-trans-4-propyl-L-2-pyrrolidinecarboxamido)-1-thio-L-threo-α-D-galacto-octopyranoside 2-(dihydrogen phosphate). The structural formula for clindamycin phosphate is represented below:

Molecular Formula: C18H34ClN2O8PS

Molecular Weight: 504.97

The chemical name for tretinoin is all-trans 3,7-dimethyl-9-(2,6,6-trimethyl-1-cyclohexen-1-yl)-2,4,6,8-nonatetraenoic acid. It is a member of the retinoid family of compounds.

The structural formula for tretinoin is represented below:

Molecular Formula: C20H28O2

Molecular Weight: 300.44

VELTIN Gel contains the following inactive ingredients: anhydrous citric acid, butylated hydroxytoluene, carbomer homopolymer (type C), edetate disodium, laureth 4, methylparaben, propylene glycol, purified water, and tromethamine.

12 CLINICAL PHARMACOLOGY

12.1 Mechanism of Action

Clindamycin:[See Microbiology (12.4).]
Tretinoin: Although the exact mode of action of tretinoin is unknown, current evidence suggests that topical tretinoin decreases cohesiveness of folliculare epithelial cells with decreased microcomedone formation. Additionally, tretinoin stimulates mitotic activity and increased turnover of follicular epithelial cells causing extrusion of the comedones.

12.3 Pharmacokinetics

In an open-label trial of 17 subjects with moderate-to-severe acne vulgaris, topical administration of approximately 3 grams of VELTIN Gel once daily for 5 days, clindamycin concentrations were quantifiable in all 17 subjects starting from 1 hour post-dose. All plasma clindamycin concentrations were ≤5.56 ng/mL on Day 5, with the exception of 1 subject who had a maximum clindamycin concentration of 8.73 ng/mL at 4 hours post-dose. There was no appreciable increase in systemic exposure to tretinoin, as compared with the baseline value. The average tretinoin concentration across all sampling times on Day 5 ranged from 1.19 to 1.23 ng/mL compared with the corresponding baseline mean tretinoin concentration range of 1.16 to 1.30 ng/mL.

12.4 Microbiology

No microbiology studies were conducted in the clinical trials with this product.

Mechanism of Action: Clindamycin binds to the 50S ribosomal subunit of susceptible bacteria and prevents elongation of peptide chains by interfering with peptidyl transfer, thereby suppressing protein synthesis. Clindamycin has been shown to have in vitro activity against Propionibacterium acnes (P. acnes), an organism that has been associated with acne vulgaris; however, the clinical significance of this activity against P. acnes was not examined in clinical trials with VELTIN Gel. P. acnes resistance to clindamycin has been documented.
Inducible Clindamycin Resistance: The treatment of acne with antimicrobials is associated with the development of antimicrobial resistance in P. acnes as well as other bacteria (e.g., Staphylococcus aureus, Streptococcus pyogenes). The use of clindamycin may result in developing inducible resistance in these organisms. This resistance is not detected by routine susceptibility testing.
Cross Resistance: Resistance to clindamycin is often associated with resistance to erythromycin.

13 NONCLINICAL TOXICOLOGY

13.1 Carcinogenesis, Mutagenesis, Impairment of Fertility

Long-term animal studies have not been performed to evaluate the carcinogenic potential of VELTIN Gel or the effect of VELTIN Gel on fertility. VELTIN Gel was negative for mutagenic potential when evaluated in an in vitroAmes Salmonella reversion assay. VELTIN Gel was equivocal for clastogenic potential in the absence of metabolic activation when tested in an in vitrochromosomal aberration assay.

Clindamycin: Once-daily dermal administration of 1% clindamycin as clindamycin phosphate in the gel vehicle (32 mg/kg/day, 13 times the recommended clinical dose based on body surface area comparison) to mice for up to 2 years did not produce evidence of tumorigenicity.

Fertility studies in rats treated orally with up to 300 mg/kg/day of clindamycin (240 times the recommended clinical dose based on body surface area comparison) revealed no effects on fertility or mating ability.

Tretinoin: In 2 independent mouse studies where tretinoin was administered topically (0.025% or 0.1%) 3 times per week for up to 2 years no carcinogenicity was observed, with maximum effects of dermal amyloidosis. However, in a dermal carcinogenicity study in mice, tretinoin applied at a dose of 5.1 mcg (1.4 times the recommended clinical dose based on body surface area comparison) 3 times per week for 20 weeks acted as a weak promoter of skin tumor formation following a single application of dimethylbenz[α]anthracene (DMBA).

In a study in female SENCAR mice, papillomas were induced by topical exposure to DMBA followed by promotion with 12-O-tetradecanoylphorbol-13-acetate or mezerein for up to 20 weeks. Topical application of tretinoin prior to each application of promoting agent resulted in a reduction in the number of papillomas per mouse. However, papillomas resistant to topical tretinoin suppression were at higher risk for pre-malignant progression.

Tretinoin has been shown to enhance photocarcinogenicity in properly performed specific studies, employing concurrent or intercurrent exposure to tretinoin and UV radiation. The photocarcinogenic potential of the clindamycin tretinoin combination is unknown. Although the significance of these studies to humans is not clear, patients should avoid exposure to sun.

The genotoxic potential of tretinoin was evaluated in an in vitroAmes Salmonella reversion test and an in vitrochromosomal aberration assay in Chinese hamster ovary cells. Both tests were negative.

In oral fertility studies in rats treated with tretinoin, the no-observed-effect-level was 2 mg/kg/day (64 times the recommended clinical dose based on body surface area comparison).

14 CLINICAL STUDIES

The safety and efficacy of VELTIN Gel, applied once daily for the treatment of acne vulgaris, was evaluated in 12-week multi-center, randomized, blinded trials in subjects 12 years and older.

Treatment response was defined as the percent of subjects who had a 2-grade improvement from baseline to Week 12 based on the Investigator’s Global Assessment (IGA) and a mean absolute change from baseline to Week 12 in 2 out of 3 (total, inflammatory and non-inflammatory) lesion counts. The IGA scoring scale used in all the clinical trials for VELTIN Gel is as follows:

0 | Clear | Normal, clear skin with no evidence of acne vulgaris.
1 | Almost Clear | Skin almost clear; rare non-inflammatory lesions present, with rare non-inflamed papules (papules must be resolving and may be hyperpigmented, though not pink-red) requiring no further treatment in the Investigator’s opinion.
2 | Mild | Some non-inflammatory lesions are present, with few inflammatory lesions (papules/pustules only, no nodulo-cystic lesions).
3 | Moderate | Non-inflammatory lesions predominate, with multiple inflammatory lesions evident; several-to-many comedones and papules/pustules, and there may or may not be 1 small nodulo-cystic lesion.
4 | Severe | Inflammatory lesions are more apparent; many comedones and papules/pustules, there may or may not be a few nodulo-cystic lesions.
5 | Very Severe | Highly inflammatory lesions predominate; variable numbers of comedones, many papules/pustules and nodulo-cystic lesions.

In Trial 1, 1,649 subjects were randomized to VELTIN Gel, clindamycin gel, tretinoin gel, and vehicle gel. The median age of subjects was 17 years and 58% were females. At baseline, subjects had an average of 71 total lesions of which the mean number of inflammatory lesions was 25.5 lesions and the mean number of non-inflammatory lesions was 45.1 lesions. The majority of subjects enrolled with a baseline IGA score of 3. The efficacy results at Week 12 are presented in Table 3.

Table 3. Efficacy Results at Week 12
Trial 1 | VELTIN Gel N = 476 | Clindamycin Gel N = 467 | Tretinoin Gel N = 464 | Vehicle Gel N = 242
Investigator’s Global Assessment
Percentage of subjects achieving 2-Grade Improvement | 36.3% | 26.6% | 26.1% | 20.2%
Percentage of subjects achieving an IGA of 0 or 1 with a 2-Grade Improvement | 33.2% | 24.0% | 22.6% | 17.8%
Inflammatory Lesions:
Mean absolute reduction | 15.5 | 14.5 | 13.9 | 11.1
Mean percentage (%) reduction | 60.4% | 56.5% | 54.5% | 43.3%
Non-inflammatory Lesions:
Mean absolute reduction | 23.2 | 19.5 | 22.1 | 17.0
Mean percentage (%) reduction | 51.0% | 42.9% | 47.3% | 36.0%
Total Lesions:
Mean absolute reduction | 38.7 | 34.0 | 36.0 | 28.1
Mean percentage (%) reduction | 55.0% | 49.0% | 50.5% | 39.1%

The safety and efficacy of clindamycin-tretinoin gel was also evaluated in 2 additional 12-week, multi-centered, randomized, blinded trials in subjects 12 years and older. A total of 2,219 subjects with mild-to-moderate acne vulgaris were treated once daily for 12 weeks. Of the 2,219 subjects, 634 subjects were treated with clindamycin-tretinoin gel. These trials demonstrated consistent outcomes.

16 HOW SUPPLIED/STORAGE AND HANDLING

How Supplied

VELTIN Gel is supplied as follows:

- 30 g aluminum tubes NDC 16110-071-30
- 60 g aluminum tubes NDC 16110-071-60

Storage and Handling

- Store at 25°C (77°F); excursions permitted from 15°C to 30°C (59°F to 86°F).
- Protect from heat.
- Protect from light.
- Protect from freezing.
- Keep out of reach of children.
- Keep tube tightly closed.

17 PATIENT COUNSELING INFORMATION

See FDA-approved patient labeling (Patient Information).

Instructions for Use

- At bedtime, the face should be gently washed with a mild soap and water. After patting the skin dry, apply VELTIN Gel as a thin layer over the entire affected area (excluding the eyes and lips).
- Patients should be advised not to use more than a pea-sized amount to cover the face and not to apply more often than once daily (at bedtime) as this will not make for faster results and may increase irritation.
- A sunscreen should be applied every morning and reapplied over the course of the day as needed. Patients should be advised to avoid exposure to sunlight, sunlamp, ultraviolet light, and other medicines that may increase sensitivity to sunlight.
- Other topical products with a strong drying effect such as abrasive soaps or cleansers may cause an increase in skin irritation with VELTIN Gel.

Skin Irritation

VELTIN Gel may cause irritation such as erythema, scaling, itching, burning, or stinging.

Colitis

In the event a patient treated with VELTIN Gel experiences severe diarrhea or gastrointestinal discomfort, VELTIN Gel should be discontinued and a physician should be contacted.

Almirall

Manufactured by DPT Laboratories, San Antonio, TX 78215
For Almirall, LLC, 101 Lindenwood Drive, Suite 400, Malvern, PA 19355
© 2019 Almirall

PATIENT INFORMATION

VELTIN™ (vel-tin)

(clindamycin phosphate and tretinoin) Gel, 1.2%/0.025%

__________________________________________________________________________________________

IMPORTANT: For use on skin only (topical use). Do not get VELTIN Gel in your mouth, eyes, or vagina.

__________________________________________________________________________________________

Read the Patient Information that comes with VELTIN Gel before you start using it and each time you get a refill. There may be new information. This leaflet does not take the place of talking with your doctor about your medical condition or your treatment.

What is VELTIN Gel?

VELTIN Gel is prescription medicine used on the skin to treat acne in people 12 years and older.

It is not known if VELTIN Gel is safe and effective in children younger than 12 years.

Who should not use VELTIN Gel?

Do not use VELTIN Gel if you have:

- Crohn’s disease
- ulcerative colitis
- had inflammation of the colon (colitis) with past antibiotic use

Talk to your doctor if you are not sure if you have one of these conditions.

What should I tell my doctor before using VELTIN Gel?

Before using VELTIN Gel, tell your doctor if you:

- have any allergies
- plan to have surgery with general anesthesia. One of the medicines in VELTIN Gel can affect how certain anesthesia medicines work.
- have any other medical conditions
- are pregnant or plan to become pregnant. It is not known if VELTIN Gel may harm your unborn baby.
- are breastfeeding or plan to breastfeed. It is not known if VELTIN Gel passes into your breast milk. One of the medicines in VELTIN Gel contains clindamycin. When clindamycin is taken by mouth or injection, it may pass into breast milk. You and your doctor should decide if you will take VELTIN Gel or breastfeed. You should not do both.

Tell your doctor about all the medicines and skin products you use. Especially tell your doctor if you take medicine that contains erythromycin. VELTIN Gel should not be used with products that contain erythromycin.

Know the medicines you take. Keep a list of your medicines and show it to your doctor and pharmacist when you get a new medicine.

How should I use VELTIN Gel?

- Use VELTIN Gel exactly as prescribed.
- Your doctor will tell you how long to use VELTIN Gel.
- Do not apply VELTIN Gel more than one time each day.
- Do not use too much VELTIN Gel, because it may irritate your skin.

Instructions for applying VELTIN Gel:

- At bedtime, wash your face gently with a mild soap; rinse with water.
- Pat the skin dry.
- Squeeze a pea-sized amount of medication onto one fingertip. Then, gently rub over the entire affected area. Do not get VELTIN Gel in your eyes, mouth, or on your lips.

What should I avoid while using VELTIN Gel?

- Limit your time in sunlight. Avoid using tanning beds or sun lamps. If you have to be in sunlight, wear a wide-brimmed hat or other protective clothing. Apply a sunscreen every morning and re-apply during the day as needed.
- Avoid wind and cold weather during treatment with VELTIN Gel. These may be irritating to your skin.
- Avoid using abrasive soaps and cleansers. These may cause increased skin irritation with VELTIN Gel.

What are the possible side effects of VELTIN Gel?

VELTIN Gel may cause serious side effects, including:

- Inflammation of the colon (colitis). Clindamycin, one of the ingredients in VELTIN Gel, can cause severe colitis that may lead to death. Stop taking VELTIN Gel and call your doctor if you develop severe watery diarrhea, or bloody diarrhea.
- Sunburn. VELTIN Gel may cause your skin to become sunburned more easily. If your face is sunburned, do not use VELTIN Gel until your sunburn is completely healed. Tretinoin, one of the medicines in VELTIN Gel, makes your skin more sensitive to sunlight. See “What should I avoid while using VELTIN Gel?”

Common side effects of VELTIN Gel include:

- Skin irritation. VELTIN Gel may cause skin irritation such as dryness, peeling, burning, or itching.

Talk to your doctor about any side effect that bothers you or that does not go away.

These are not all the side effects with VELTIN Gel. Ask your doctor or pharmacist for more information.

Call your doctor for medical advice about side effects. You may report side effects to FDA at 1-800-FDA-1088.

How should I store VELTIN Gel?

- Store VELTIN Gel at room temperature, between 59°F to 86°F (15°C to 30°C).
- Protect from freezing.
- Keep VELTIN Gel away from heat and light.
- Keep VELTIN Gel and all medicines out of the reach of children.

General information about VELTIN Gel

Medicines are sometimes prescribed for purposes other than those listed in the patient information leaflet. Do not use VELTIN Gel for a condition for which it was not prescribed. Do not give VELTIN Gel to other people, even if they have the same symptoms you have. It may harm them.

This patient information leaflet summarizes the most important information about VELTIN Gel. If you would like more information, talk with your doctor. You can also ask your pharmacist or doctor for information about VELTIN Gel that is written for healthcare professionals. For more information call 1-866-665-2782.

What are the ingredients in VELTIN Gel?

Active Ingredients: clindamycin phosphate and tretinoin

Inactive ingredients: anhydrous citric acid, butylated hydroxytoluene, carbomer homopolymer (type C), edetate disodium, laureth 4, methylparaben, propylene glycol, purified water, and tromethamine.

This Patient Information has been approved by the U.S. Food and Drug Administration.

Almirall

Manufactured by DPT Laboratories, San Antonio, TX 78215
For Almirall, LLC, 101 Lindenwood Drive, Suite 400, Malvern, PA 19355
© 2019 Almirall
Revised: 06/2019